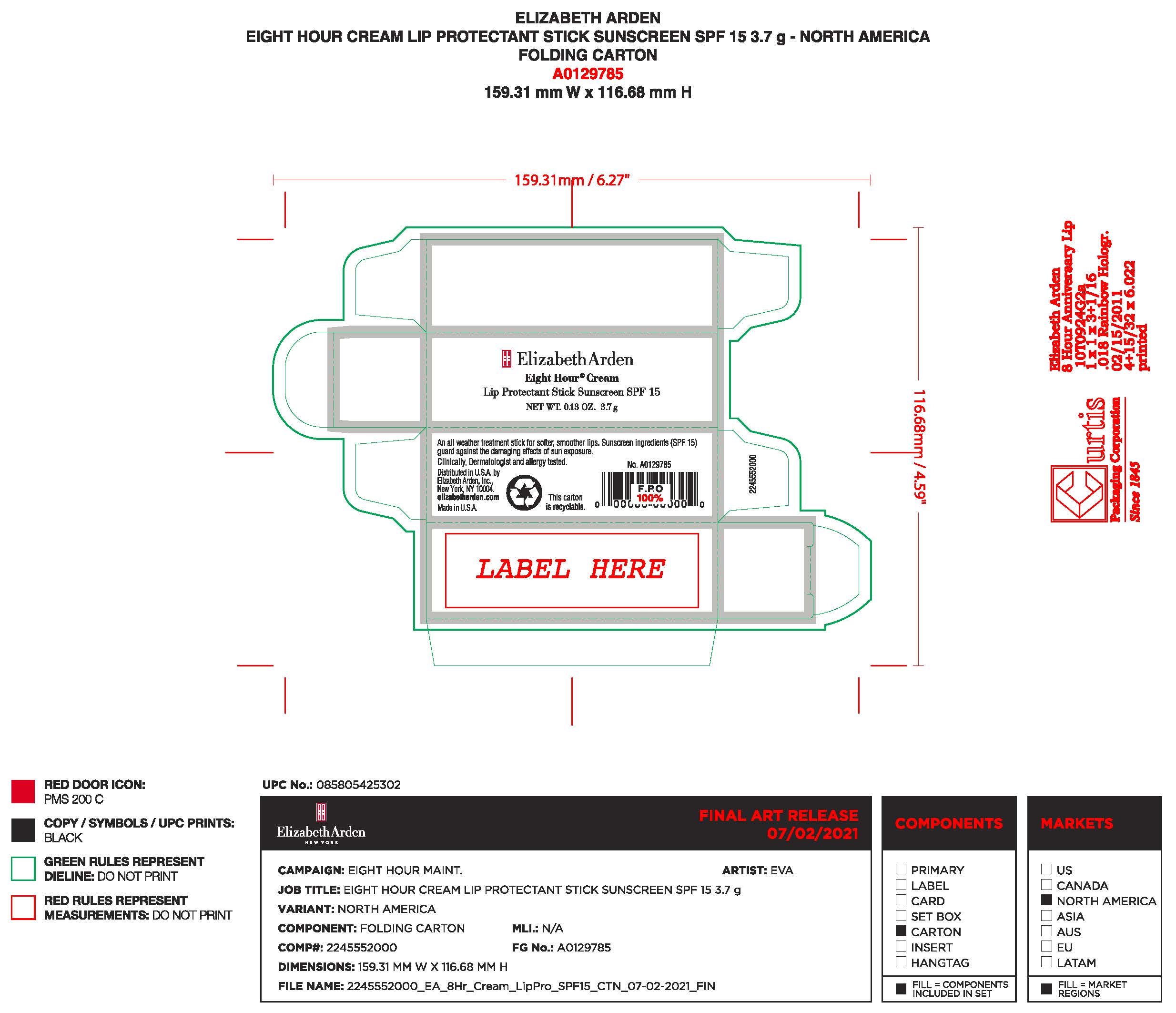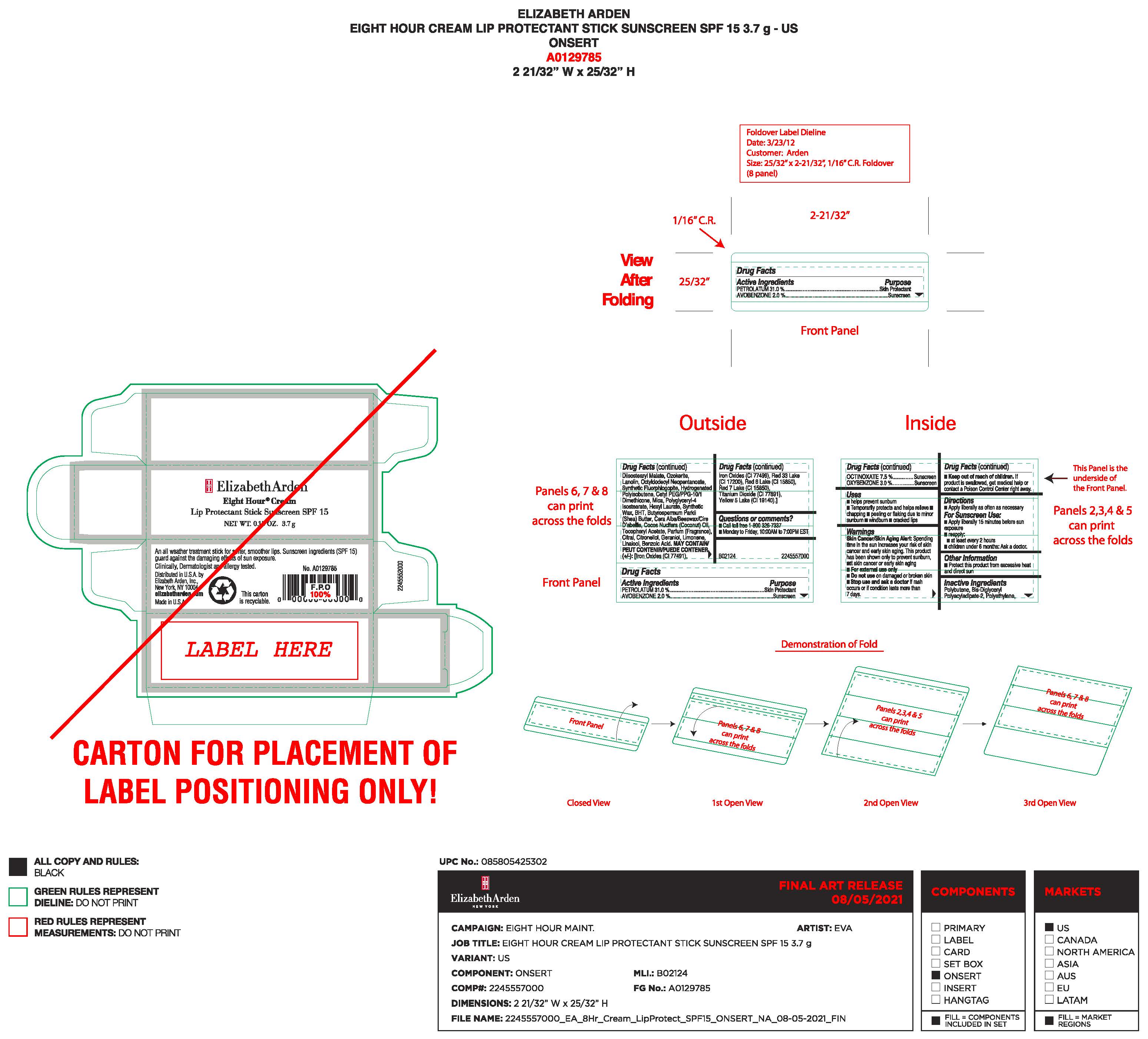 DRUG LABEL: ELIZABETH ARDEN EIGHT HR PROTECTANT CLEAR
NDC: 10967-676 | Form: LIPSTICK
Manufacturer: REVLON CONSUMER PRODUCTS CORP
Category: otc | Type: HUMAN OTC DRUG LABEL
Date: 20241230

ACTIVE INGREDIENTS: PETROLATUM 1.147 g/3.7 g; OCTINOXATE 0.2775 g/3.7 g; OXYBENZONE 0.111 g/3.7 g; AVOBENZONE 0.074 g/3.7 g
INACTIVE INGREDIENTS: MICA; SYNTHETIC WAX (1200 MW); BIS-DIGLYCERYL POLYACYLADIPATE-2; DIISOSTEARYL MALATE; CERESIN; OCTYLDODECYL NEOPENTANOATE; CETYL PEG/PPG-10/1 DIMETHICONE (HLB 2); POLYGLYCERYL-4 ISOSTEARATE; SYNTHETIC BEESWAX; COCONUT OIL; POLYBUTENE (1400 MW); FRAGRANCE 13576; HIGH DENSITY POLYETHYLENE; LANOLIN; BUTYROSPERMUM PARKII (SHEA) BUTTER UNSAPONIFIABLES; BENZOIC ACID; BUTYLATED HYDROXYTOLUENE; HEXYL LAURATE; MAGNESIUM POTASSIUM ALUMINOSILICATE FLUORIDE; POLYISOBUTYLENE (1000 MW); .ALPHA.-TOCOPHEROL ACETATE

ELIZABETH ARDEN EIGHT HOUR CREAM LIP PROTECTANT STICK SUNSCREEN SPF 15- CLEAR

ACTIVE INGREDIENTS

ACTIVE INGREDIENT PURPOSE

PETROLATUM 31.0% SKIN PROTECTANT

AVOBENZONE 2.0% SUNSCREEN

OCTINOXATE 7.5% SUNSCREEN

OXYBENZONE 3.0% SUNSCREEN

USES

- helps prevent sunburn
- Temporarily protects and helps relieve
- chapping
- peeling or flaking due to minor sunburn
- windburn
- cracked lips

Warnings

Skin Cancer/Skin Aging Alert: spending time in the sun increases your risk of skin cancer and early skin aging. This product has been shown only to prevent sunburn, not skin cancer or early skin aging.

- For external use only
- Do not use on damaged or broken skin
- Stop use and ask a doctor if rash occurs or if condition lasts more than 7 days.
- Keep out of reach of children. If product is swallowed get medical help or contact a Poison Control Center right away.

Directions

- Apply liberally as often as necessary

For Sunscreen Use:

- Apply liberally 15 minutes before sun exposure
- reapply:
- atleast every 2 hours
- children under 6 months: Ask a doctor.

Other Information

- Protect this product from excessive heat and direct sun

Inactive ingedients

Polybutene, Bis-Diglyceryl Polyacyladipate-2, Polyethylene, Diisostearyl Malate, Ozokerite, Lanolin, Octyldodecyl Neopentanoate, Synthetic Fluorphlogopite, Hydrogenated Polyisobutene, Cetyl PEG/PPG-10/1 Dimethicone, Mica, Polyglyceryl-4 Isostearate, Hexyl Laurate, Synthetic Wax, BHT, Butyrospermum Parkii (Shea) Butter, Cera Alba/Beeswax/Cire D’abeille, Cocos Nucifera (Coconut) Oil, Tocopheryl Acetate, Parfum (Fragrance), Citral, Citronellol, Geraniol, Limonene, Linalool, Benzoic Acid. MAY CONTAIN/PEUT CONTENIR/PUEDE CONTENER (+/-): [Iron Oxides (CI 77491), Iron Oxides (CI 77499), Red 33 Lake (CI 17200), Red 6 Lake (CI 15850), Red 7 Lake (CI 15850), Titanium Dioxide (CI 77891), Yellow 5 Lake (CI 19140).]

Questions or Comments?

- Call toll free 1-800-326-7337
- Monday to Friday, 10:00AM to 7:00PM EST

Skin protectant Directions

Apply liberally as often as necessary

Keep out of reach of children

If product is swallowed, get medical help or contact poison control center right away.

Uses

- Helps prevent sunburn
- Temporarily protects and helps relieve
- Chapping
- Peeling or flaking due to minor sunburn
- Windburn
- Cracked lips

Directions and Usage

- Apply liberally as often as necessary
- For sunscreen use: apply liberally 15 minutes before sun exposure
- Reapply: atleast every 2 hours
- Children under 6 months: ask a doctor